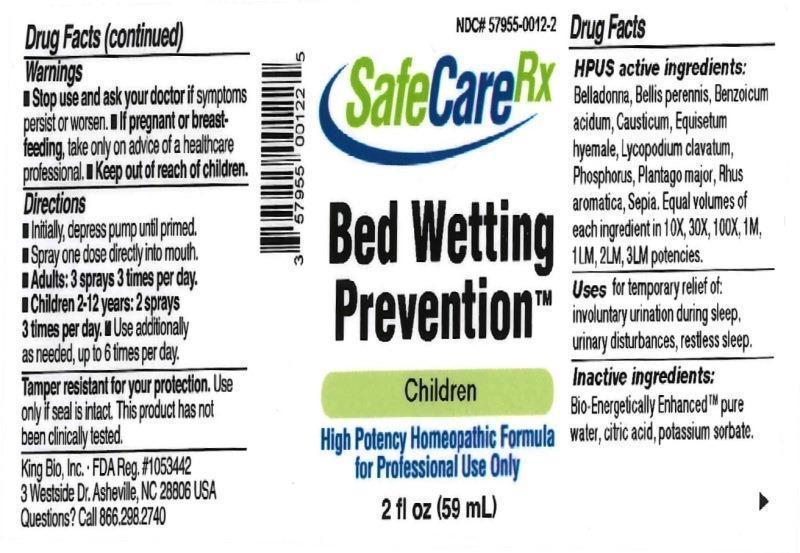 DRUG LABEL: Bed Wetting prevention
NDC: 57955-0012 | Form: LIQUID
Manufacturer: King Bio Inc.
Category: homeopathic | Type: HUMAN OTC DRUG LABEL
Date: 20161108

ACTIVE INGREDIENTS: ATROPA BELLADONNA 10 [hp_X]/59 mL; BELLIS PERENNIS 10 [hp_X]/59 mL; BENZOIC ACID 10 [hp_X]/59 mL; CAUSTICUM 10 [hp_X]/59 mL; EQUISETUM HYEMALE 10 [hp_X]/59 mL; LYCOPODIUM CLAVATUM SPORE 10 [hp_X]/59 mL; PHOSPHORUS 10 [hp_X]/59 mL; PLANTAGO MAJOR 10 [hp_X]/59 mL; RHUS AROMATICA ROOT BARK 10 [hp_X]/59 mL; SEPIA OFFICINALIS JUICE 10 [hp_X]/59 mL
INACTIVE INGREDIENTS: WATER; ANHYDROUS CITRIC ACID; POTASSIUM SORBATE

Bed Wetting Prevention

ACTIVE INGREDIENT

Drug Facts__________________________________________________________________________________________________________

HPUS active ingredients: Belladonna, Bellis perennis, Benzoicum acidum, Causticum, Equisetum hyemale, Lycopodium clavatum, Phosphorus, Plantago major, Rhus aromatica, Sepia. Equal volumes of each ingredient in 10X, 30X, 100X, 1M, 1LM, 2LM, 3LM potencies.

INDICATIONS AND USAGE

Uses for temporary relief of: involuntary urination during sleep, urinary disturbances, restless sleep.

Inactive Ingredients:

Bio-Energetically Enhanced™ pure water, citric acid and potassium sorbate.

Warnings

- Stop use and ask your doctor if symptoms persist or worsen.
- If pregnant or breast-feeding, take only on advice of a healthcare professional.

- Keep out of reach of children.

Directions

- Initially, depress pump until primed.
- Spray one dose directly into mouth.
- Adults: 3 sprays 3 times per day.
- Children 2-12 years: 2 sprays 3 times per day.
- Use additionally as needed, up to 6 times per day.

OTHER SAFETY INFORMATION

Tamper resistant for your protection. Use only if safety seal is intact. This product has not been clinically tested.

PURPOSE

Uses for temporary relief of:

- involuntary urination during sleep
- urinary disturbances
- restless sleep